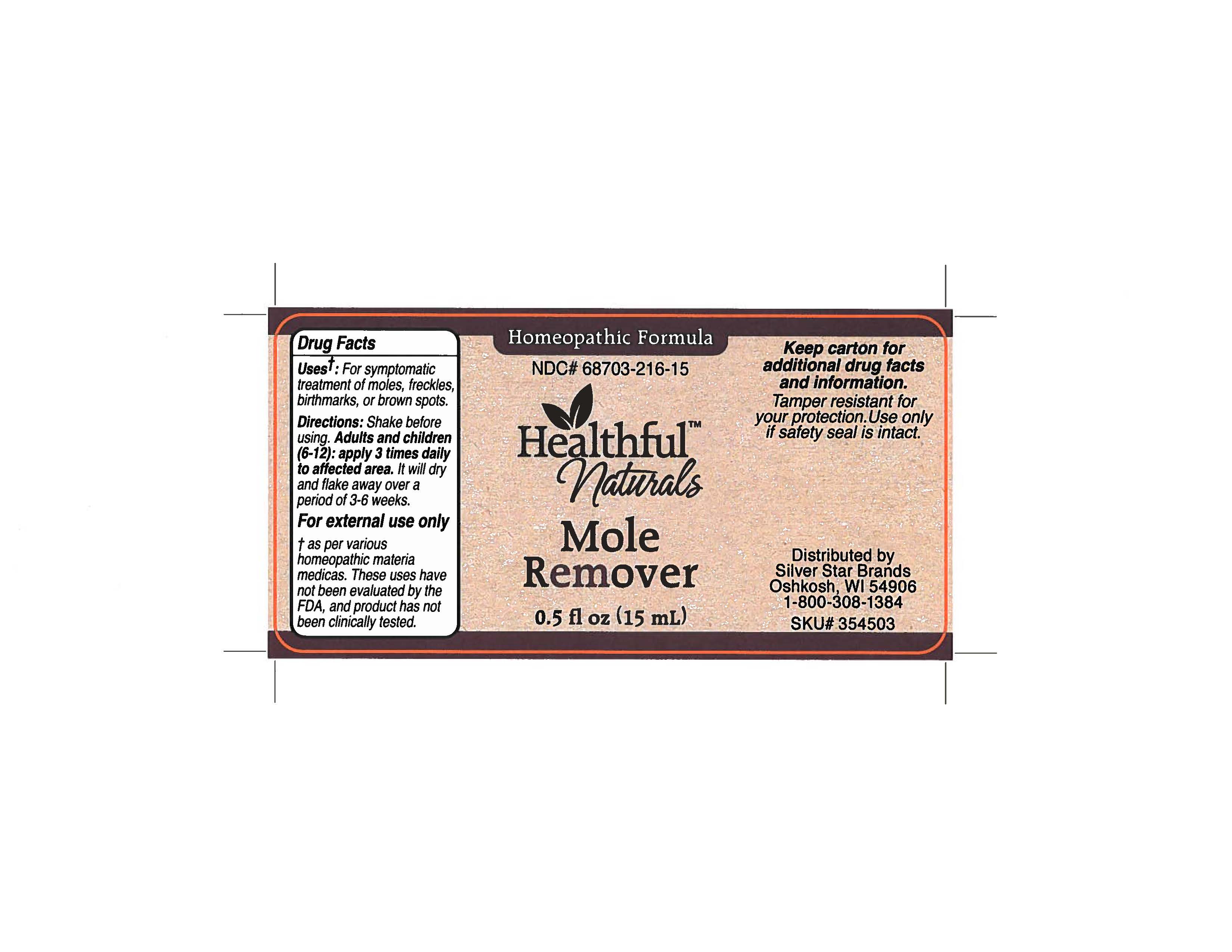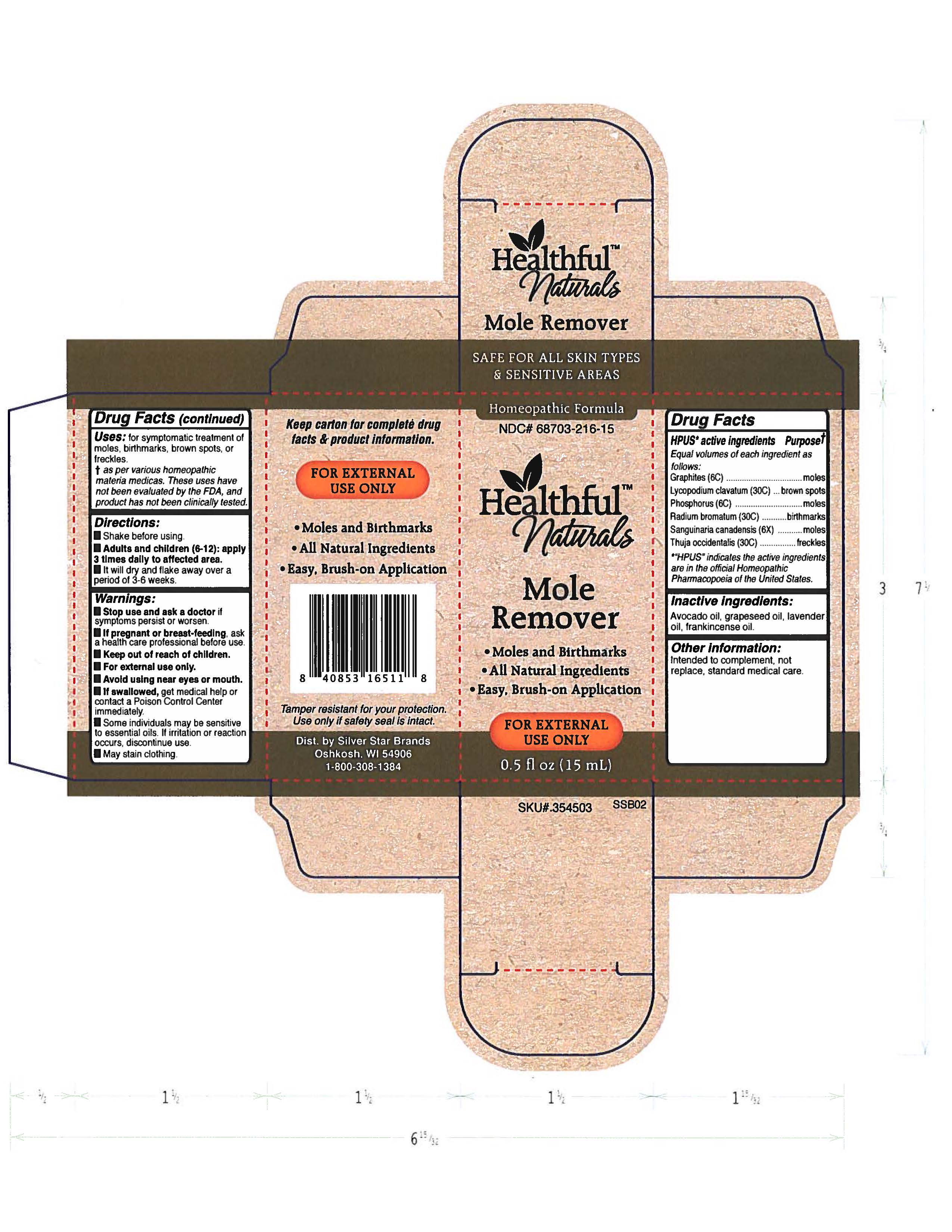 DRUG LABEL: Healthful Naturals Mole Remover
NDC: 68703-216 | Form: LIQUID
Manufacturer: Healthful™ Naturals Mole Remover - 15 ml
Category: homeopathic | Type: HUMAN OTC DRUG LABEL
Date: 20230304

ACTIVE INGREDIENTS: PHOSPHORUS 6 [hp_C]/15 mL; SANGUINARIA CANADENSIS ROOT 6 [hp_X]/15 mL; GRAPHITE 6 [hp_C]/15 mL; LYCOPODIUM CLAVATUM SPORE 30 [hp_C]/15 mL; RADIUM BROMIDE 30 [hp_C]/15 mL; THUJA OCCIDENTALIS LEAFY TWIG 30 [hp_C]/15 mL
INACTIVE INGREDIENTS: FRANKINCENSE OIL; GRAPE SEED OIL; AVOCADO OIL; LAVENDER OIL

Healthful™ Naturals Mole Remover - 15 ml

HPUS* active ingredients Purpose +

Equal volumes of each ingredient as follows:

Graphites (6C), Lycopodium clavatum (30C), Phosphorus (6C), Radium bromatum (30C), Sanguinaria canadensis (6X), Thuja occidentalis

*"HPUS" indicates the active ingredients are in the offical Homeopathic Pharmacopoeia of the United States.

Uses:

Uses: for symptomatic treatment of moles, birthmarks, brown spots, or freckles.

+ as per various homeopathic materia medicas. These uses have not been evaluted by the FDA, and product has not been clinically tested.

Warnings

Stop use and ask a doctor if symptoms persist or worsen.

If pregnant or breast-feeding, ask a healthcare professional before use.

Keep out of reach of children.

For external use only.

Avoid using near eyes or mouth.

If swallowed, get medical help or contact a Poison Control Center immediately.

Sme individuals may be sensitive to essential oils. If irritation or reaction occurs, discontinue use.

May stain clothing.

Directions

Shake before using.

Adults and children (6-12): apply 3 times daily to affected area.

It will dry and flake away over a period of 3-6 weeks.

OTHER SAFETY INFORMATION

Intended to complement, not replace, standard medical care.

Inactive Ingredients

Avocado oil, grapeseed oil, lavender oil, frankincense oil.

Keep out of reach of children.

PREGNANCY OR BREAST FEEDING

If pregnant or breast-feeding, ask a health care professional before use.

HPUS* active ingredients Purpose

Equal volumes of each ingredient as follows:

Graphites......................................moles

Lycopodium clavatum.................brown spots

Phosphorus.................................moles

Radium bromatum......................birthmarks

Sanguinaria canadensis.............moles

Thuja occidentalis.......................freckles